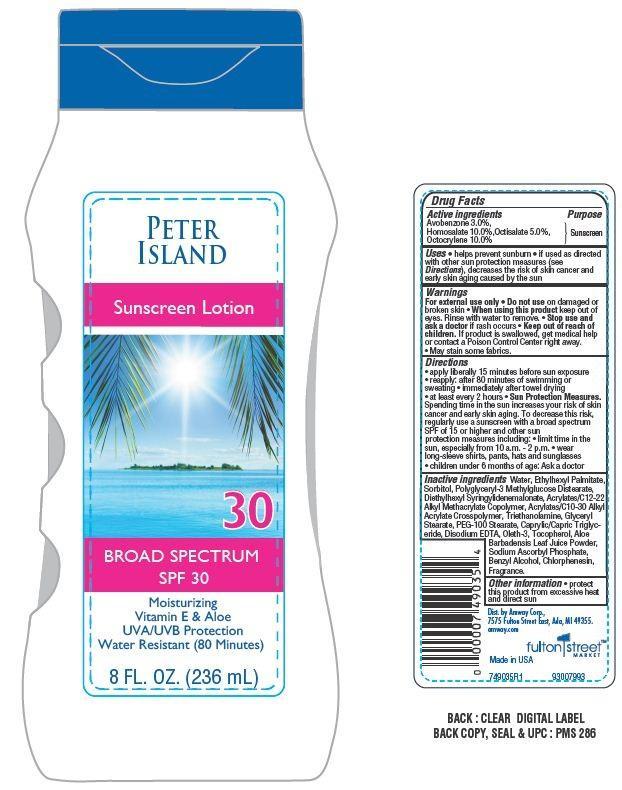 DRUG LABEL: Peter Island Continous sunscreen
NDC: 10056-711 | Form: LOTION
Manufacturer: Access Business Group LLC
Category: otc | Type: HUMAN OTC DRUG LABEL
Date: 20130709

ACTIVE INGREDIENTS: OCTOCRYLENE 10 g/100 g; AVOBENZONE 3 g/100 g; OCTISALATE 5 g/100 g; HOMOSALATE 10 1/100 g
INACTIVE INGREDIENTS: WATER; ETHYLHEXYL PALMITATE; SORBITOL; DIETHYLHEXYL SYRINGYLIDENEMALONATE; ALOE VERA LEAF; TROLAMINE; GLYCERYL MONOSTEARATE; PEG-100 STEARATE; TRICAPRIN; EDETATE DISODIUM; OLETH-3; TOCOPHEROL; SODIUM ASCORBYL PHOSPHATE; BENZYL ALCOHOL; CHLORPHENESIN

Drug Facts

Active ingredients

Avobenzone 3.0%,

Homosalate 10.0%

Octisalate 5.0%

Octocrylene 10.0%

Purpose

Sunscreen

Warnings

For external use only

Do not use on damaged skin or broken skin

Stop use and ask a doctor

if rash occurs

When using this product

keep out of eyes. Rinse with water to remove.

keep out of reach of children

if product is swallowed, get medical help or contact a Poison Control Center right away.

- May stain some fabrics.

DIRECTIONS:

- apply liberally 15 minutes before sun exposure
- reapply: after 80 minutes of swimming or sweating
- immediately after towel drying
- at least every 2 hours.

Sun protection measures:

- Spending time in the sun increase your risk of skin cancer and early skin aging To decrease this risk, regularly use a sunscreen with a broad spectrum SPF of 15 or higher and other sun protection measures including:
- limit time in the sun, especially from 10 a.m.- 2 p.m
- wear long -sleeve shirts, pants, hats and sunglasses
- children under 6 months of age:Ask a doctor

Other Information

protect this product from excessive heat and direct sun

Uses

- helps prevent sunburn
- if used as directed with other sun protection measures (see directions), decrease the risk of skin cancer and early skin aging caused by the sun.

Principal Display Panel

PETER

ISLAND

Sunscreen Lotion

30

BROAD SPECTRUM

SPF 30

Moisturizing

Vitamion E and Aloe

UVA/UVB Protection

Water Resistant (80 minutes)

8 FL. OZ. (236 mL)

Inactive Ingredients

water, Ethylhexyl Palmitate, Sorbitol, Polyglyceryl-3 Methylglucoase Distearate, Diethylhexyl Syringyldenemalonate, Acrylates/C12-22 Alkyl methcrylate, Copolymer, Acrylates/C10-30 Alkyl Acrylate Crosspolymer, Triethanolamine, Glyceryl Stearate, PEG_100 Stearate, Caprylic/Capric Triglyceride, Disodium EDTA, Oleth-3, Tocopherol, Aloe Barbadensis Leaf Juice Powder, Sodium Ascorbyl Phosphate, Benzyl Alcohol, Chlorphenesin, Fragrance.